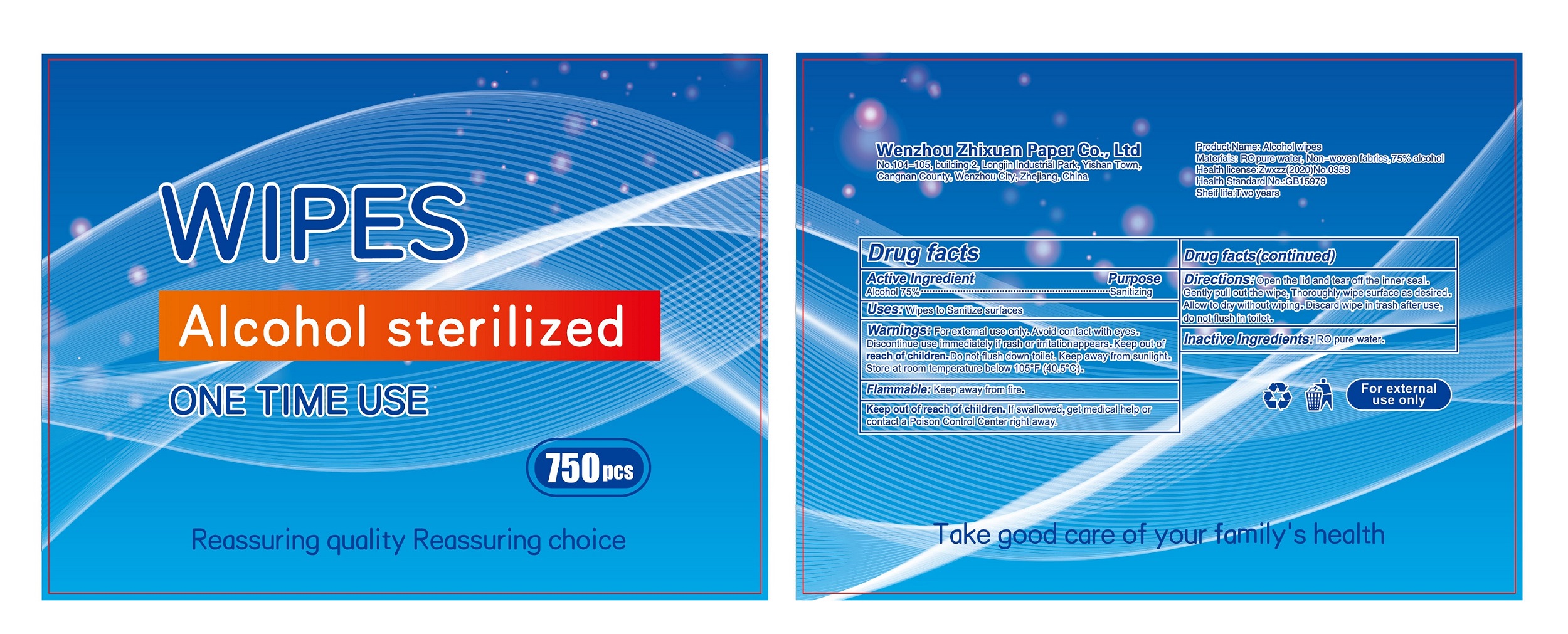 DRUG LABEL: Alcohol Wipes
NDC: 79295-001 | Form: CLOTH
Manufacturer: Wenzhou Zhixuan Paper Co., Ltd
Category: otc | Type: HUMAN OTC DRUG LABEL
Date: 20200701

ACTIVE INGREDIENTS: ALCOHOL 75 mL/100 mL
INACTIVE INGREDIENTS: WATER

79295-001 Alcohol Wipes 75% Alcohol

Active Ingredient

Ethyl Alcohol 75%

Purpose

Sanitizing

USE

wipes to Sanitize surfaces

Warning

For external use only

Avoid contact with eyes.
Discontinue use immediately if rash or irritationappears.Keep out of
reach of children

Do not flush down toilet. Keep away from sunlight.
Store at room temperature below 105F(40.5C)
Flammablea:Keep away from fire.

Keep out of reach of children

lf swallowed,get medical help or contacta Poison Control Cente right away.

Directions

open the lid and tear off the inner seal.
Gently pull out the wipe,Thoroughly wipe surface as desired.
Allow to dry without wiping.Discard wipe in trash after use,
do not flush in toilet.

Inactive ingredients

RO pure water